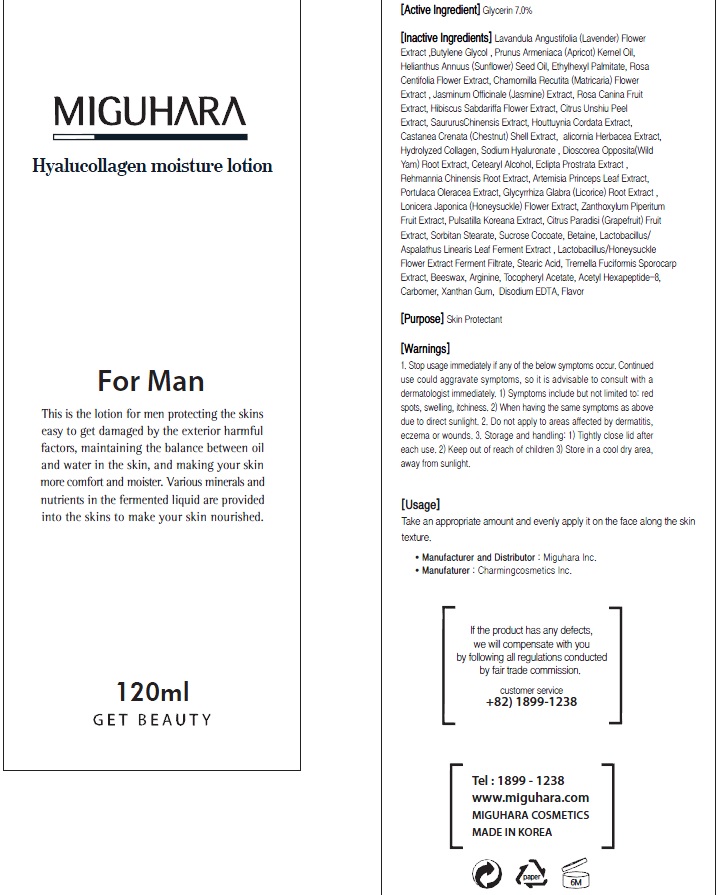 DRUG LABEL: Hyalucollagen Moisture
NDC: 70380-210 | Form: LOTION
Manufacturer: MIGUHARA
Category: otc | Type: HUMAN OTC DRUG LABEL
Date: 20160222

ACTIVE INGREDIENTS: Glycerin 10.5 g/150 mL
INACTIVE INGREDIENTS: LAVANDULA ANGUSTIFOLIA FLOWER; Butylene Glycol

ACTIVE INGREDIENT

Active Ingredient: Glycerin 7.0%

INACTIVE INGREDIENT

Inactive Ingredients: Lavandula Angustifolia (Lavender) Flower Extract, Butylene Glycol , Prunus Armeniaca (Apricot) Kernel Oil, Helianthus Annuus (Sunflower) Seed Oil, Ethylhexyl Palmitate, Rosa Centifolia Flower Extract, Chamomilla Recutita (Matricaria) Flower Extract , Jasminum Officinale (Jasmine) Extract, Rosa Canina Fruit Extract, Hibiscus Sabdariffa Flower Extract, Citrus Unshiu Peel Extract, Saururus Chinensis Extract, Houttuynia Cordata Extract, Castanea Crenata (Chestnut) Shell Extract, Salicornia Herbacea Extract, Hydrolyzed Collagen, Sodium Hyaluronate , Dioscorea Opposita (Wild Yam) Root Extract, Cetearyl Alcohol, Eclipta Prostrata Extract , Rehmannia Chinensis Root Extract, Artemisia Princeps Leaf Extract, Portulaca Oleracea Extract, Glycyrrhiza Glabra (Licorice) Root Extract , Lonicera Japonica (Honeysuckle) Flower Extract, Zanthoxylum Piperitum Fruit Extract, Pulsatilla Koreana Extract, Citrus Paradisi (Grapefruit) Fruit Extract, Sorbitan Stearate, Sucrose Cocoate, Betaine, Lactobacillus/Aspalathus Linearis Leaf Ferment Extract , Lactobacillus/Honeysuckle Flower Extract Ferment Filtrate, Stearic Acid, Tremella Fuciformis Sporocarp Extract, Beeswax, Arginine, Tocopheryl Acetate, Acetyl Hexapeptide-8, Carbomer, Xanthan Gum, Disodium EDTA, Flavor

PURPOSE

Purpose: Skin Protectant

WARNINGS

1. Stop usage immediately if any of the below symptoms occur. Continued use could aggravate symptoms, so it is advisable to consult with a dermatologist immediately. 1) Symptoms include but not limited to: red spots, swelling, itchiness. 2) When having the same symptoms as above due to direct sunlight. 2. Do not apply to areas affected by dermatitis, eczema or wounds. 3. Storage and handling: 1) Tightly close lid after each use. 2 Keep out of reach of children 3) Store in a cool dry area, away from sunlight

KEEP OUT OF REACH OF CHILDREN

Usage

Usage: Take an appropriate amount and evenly apply it on the face along the skin texture.

Usage

Usage: Take an appropriate amount and evenly apply it on the face along the skin texture.